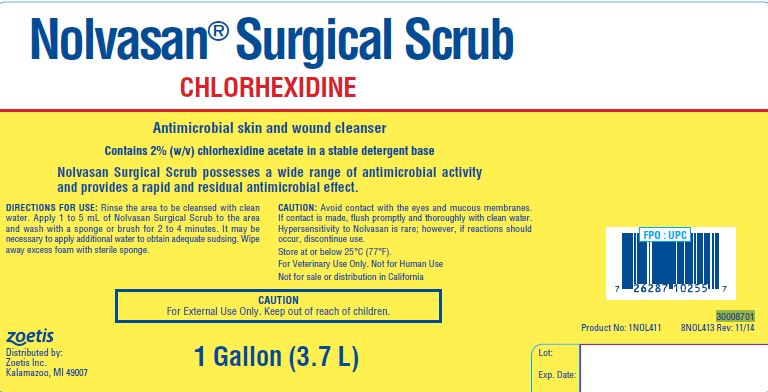 DRUG LABEL: Nolvasan Surgical Scrub
NDC: 54771-8701 | Form: SOLUTION
Manufacturer: Zoetis Inc.
Category: animal | Type: OTC ANIMAL DRUG LABEL
Date: 20220907

ACTIVE INGREDIENTS: CHLORHEXIDINE ACETATE 20 mg/1 mL

Nolvasan® Surgical Scrub

DESCRIPTION

Nolvasan® Surgical Scrub
CHLORHEXIDINE
Antimicrobial skin and wound cleanser
Contains 2% (w/v) chlorhexidine acetate in a stable detergent base
Nolvasan Surgical Scrub possesses a wide range of antimicrobial activity and provides a rapid and residual antimicrobial effect.

DIRECTIONS FOR USE

Rinse the area to be cleansed with clean water. Apply 1 to 5 mL of Nolvasan Surgical Scrub to the area and wash with a sponge or brush for 2 to 4 minutes. It may be necessary to apply additional water to obtain adequate sudsing. Wipe away excess foam with sterile sponge.

CAUTION

Avoid contact with the eyes and mucous membranes. If contact is made, flush promptly and thoroughly with clean water. Hypersensitivity to Nolvasan is rare; however, if reactions should occur, discontinue use.

Store at or below 25°C (77°F).
For Veterinary Use Only. Not for Human Use
Not for sale or distribution in California

CAUTION

For External Use Only. Keep out of reach of children.

zoetis
Distributed by:
Zoetis Inc.
Kalamazoo, MI 49007
1 Gallon (3.7 L)
30008701